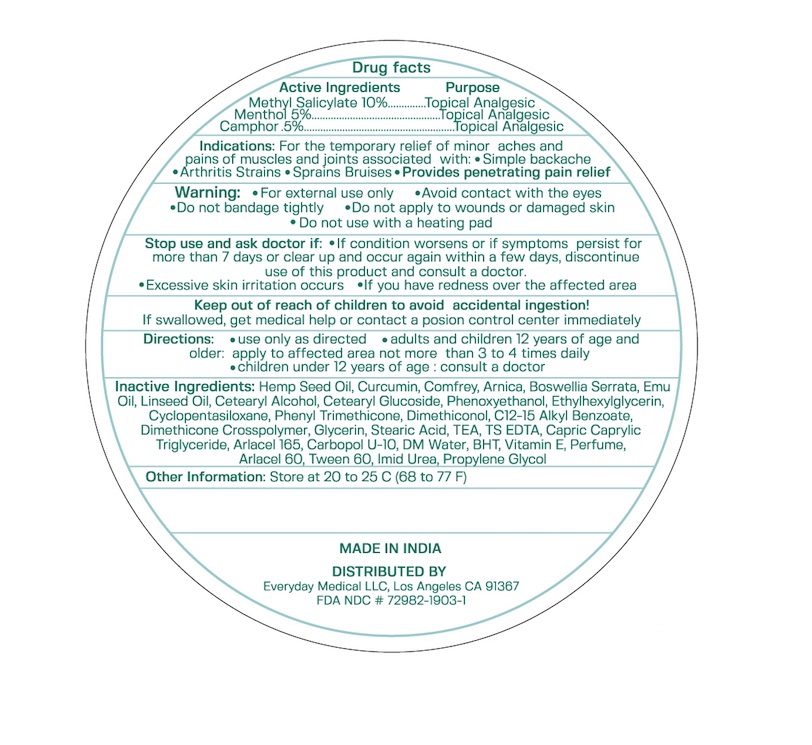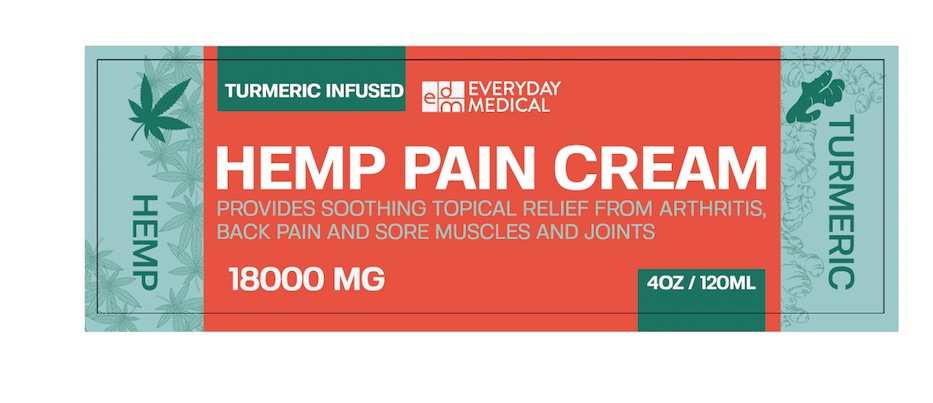 DRUG LABEL: Turmeric Infused Hemp Pain Cream
NDC: 72982-1906 | Form: CREAM
Manufacturer: Everyday Medical LLC
Category: otc | Type: HUMAN OTC DRUG LABEL
Date: 20200113

ACTIVE INGREDIENTS: MENTHOL 5 g/100 g; CAMPHOR (NATURAL) 0.5 g/100 g; METHYL SALICYLATE 10 g/100 g
INACTIVE INGREDIENTS: HEMP; LINSEED OIL; WATER; ARNICA MONTANA; BOSWELLIA SERRATA WHOLE; CURCUMIN; ALPHA-TOCOPHEROL ACETATE; CETOSTEARYL ALCOHOL; STEARIC ACID; COMFREY; EMU OIL; CETETH-20

Tumeric Infused Hemp Pain Cream

Active Ingredients Purpose

Methyl Salicylate 10% Topical Analgesic

Menthol 5% Topical Analgesic

Camphor 0.5% Topical Analgesic

PURPOSE

Topical analgesic

INDICATIONS AND USAGE

temporarily relieves minor pain associated with

- arthritis
- simple backache
- muscle strains
- bruises
- sprains
- cramps

Warnings

For external use only

When using this product: Use only as directed

- do not bandage tightly or use with a heating pad
- avoid contact with eyes and mucous membranes
- do not apply to wounds or damaged, broken or irritated skin
- if severe burning sensation occurs, discontinue use immediately

Stop use and ask a doctor if

- condition worsens
- redness is present
- irritation develops

Keep out of reach of children. If swallowed get medical help or contact a Poison Control Center right away

DOSAGE AND ADMINISTRATION

- Use only as directed
- Adults and children 12 years of age and older apply to affected area not more than 3 to 4 times daily
- Children under the age of 12 years of age consult a doctor

INACTIVE INGREDIENT

- Comfrey extract
- Arnica extract
- Boswellia serrata extract
- Emu oil
- Linseed oil
- Curcumin
- Vitamin E acetate oil
- Cetomacrogol 1000
- Ceto steryl alcohol
- Carbopol 2020
- Light liquid parafin
- White soft paraffin
- BHA
- BHT
- Hemp
- Glyceryl mono stearate
- Sodium meta bisulphate
- Simethicone
- Purified water